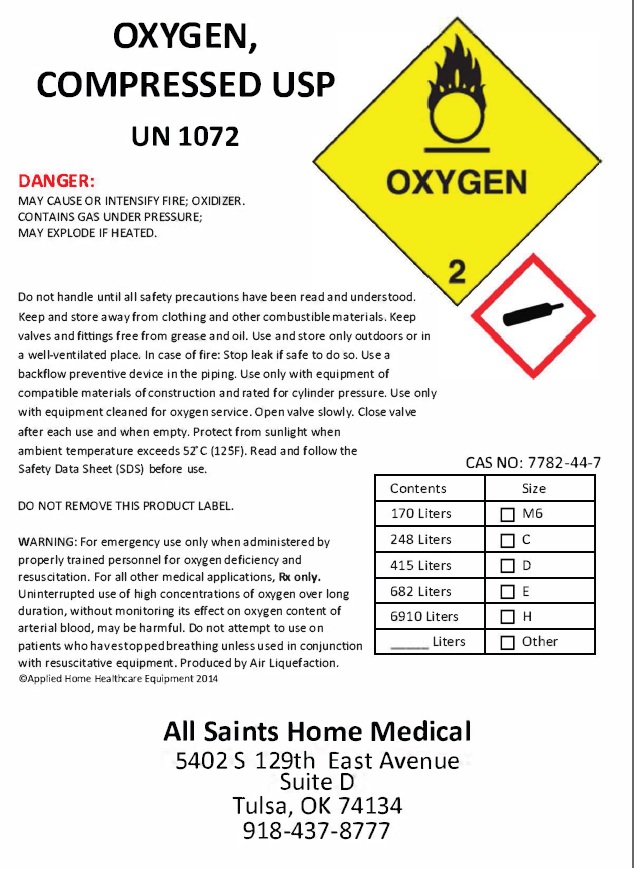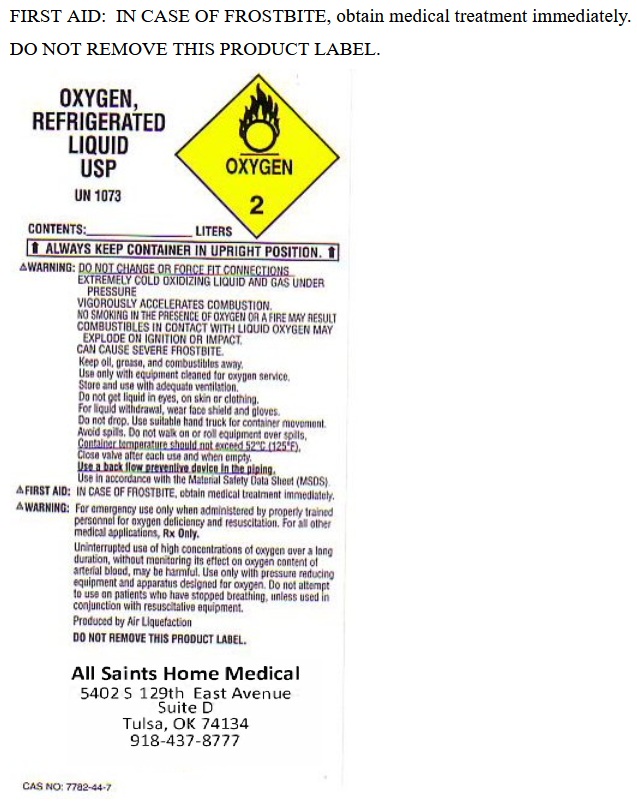 DRUG LABEL: Oxygen
NDC: 54202-001 | Form: GAS
Manufacturer: All Saints Home Medical
Category: prescription | Type: HUMAN PRESCRIPTION DRUG LABEL
Date: 20250603

ACTIVE INGREDIENTS: Oxygen 99 L/100 L

GENERAL WARNINGS AND PRECAUTIONS

Warning: For emergency use only when administered by properly trained personnel for oxygen deficiency and resuscitation. For all other medical applications, Rx Only. Uninterrupted use of high concentrations of oxygen over a long duration, without measuring its effect on oxygen content of arterial blood, may be harmful. Use only with pressure reducing equipment and apparatus designed for oxygen. Do not attempt to use on patients who have stopped breathing, unless used in conjunction with resuscitative equipment.

OXYGEN COMPRESSED LABEL

OXYGEN,
COMPRESSED USP
UN 1072

DANGER:
MAY CAUSE OR INTENSIFY FIRE; OXIDIZER.
CONTAINS GAS UNDER PRESSURE;
MAY EXPLODE IF HEATED.

Do not handle until all safety precautions have been read and understood.
Keep and store away from clothing and other combustible materials. Keep
valves and fittings free from grease and oil. Use and store only outdoors or in
a well-ventilated place. In case of fire: Stop leak if safe to do so. Use a
backflow preventive device in the piping. Use only with equipment of
compatible materials of construction and rated for cylinder pressure. Use only
with equipment cleaned for oxygen service. Open valve slowly. Close valve
after each use and when empty. Protect from sunlight when
ambient temperature exceeds 52"C (12SF). Read and follow the

Safety Data Sheet (SOS) before use.

CAS NO: 7782-44-7

DO NOT REMOVE THIS PRODUCT LABEL.

WARNING: For emergency use only when administered by
properly trained personnel for oxygen deficiency and
resuscitation. For all other medical applications, Rx only.
Uninterrupted use of high concentrations of oxygen over long
duration, without monitoring its effect on oxygen content of
arterial blood, may be harmful. Do not attempt to use on
patients who have stopped breathing unless used in conjunction
with resuscitative equipment. Produced by Air Liquefaction.
©Applied Home Healthcare Equipment 2014

All Saints Home Medical
5402 S 129th East Avenue
Suite D
Tulsa, OK 74134
918-437-8777

OXYGEN REFRIGERATED LIQUID LABEL

OXYGEN, REFRIGERATED LIQUID USP UN 1073

CONTENTS: ________________ LITERS

ALWAYS KEEP CONTAINER IN UPRIGHT POSITION.

WARNING; DO NOT CHANGE OR FORCE FIT CONNECTIONS. EXTREMELY COLD OXIDIZING LIQUID AND GAS UNDER PRESSURE. VIGOROUSLY ACCELERATES COMBUSTION. NO SMOKING IN THE PRESENCE OF OXYGEN OR A FIRE MAY RESULT. COMBUSTIBLES IN CONTACT WITH LIQUID OXYGEN MAY EXPLODE ON IGNITION OR IMPACT. CAN CAUSE SEVERE FROSTBITE.

Keep oil, grease, and combustibles away. Use only with equipment cleaned for oxygen service. Store and use with adequate ventilation. Do not get liquid in eyes, on skin or clothing. For liquid withdrawal, wear face shield and gloves. Do not drop. Use suitable hand truck for container movement. Avoid spills. Do not walk on or roll equipment over spills. Container temperature should not exceed 52 C (125 F). Close valve after each use and when empty. Use a back flow preventative device in the piping. Use in accordance with the Material Safety Data Sheet (MSDS).